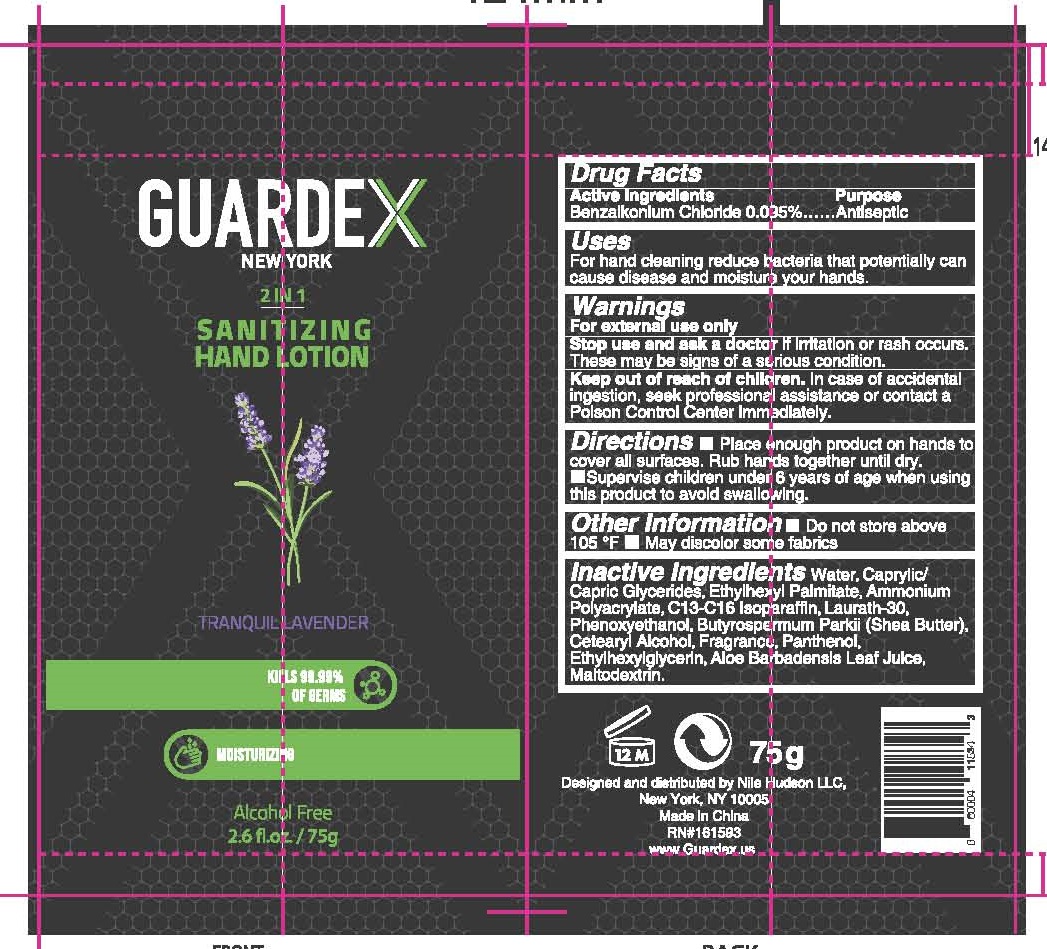 DRUG LABEL: GUARDEX SANITIZING HAND
NDC: 81353-126 | Form: LOTION
Manufacturer: Nile Hudson LLC
Category: otc | Type: HUMAN OTC DRUG LABEL
Date: 20201226

ACTIVE INGREDIENTS: BENZALKONIUM CHLORIDE 0.95 g/1 mL
INACTIVE INGREDIENTS: MALTODEXTRIN; MEDIUM-CHAIN TRIGLYCERIDES; WATER; ETHYLHEXYL PALMITATE; SHEA BUTTER; ALOE VERA LEAF; LAURETH-30; PHENOXYETHANOL; C13-16 ISOPARAFFIN; AMINOMETHYLPROPANOL; PANTHENOL; CETOSTEARYL ALCOHOL; ETHYLHEXYLGLYCERIN

GUARDEX
2 IN 1 SANITIZING HAND LOTION
TRANQUIL LAVENDER

Active Ingredients

Benzalkonium Chloride 0.095%

Purpose

Antiseptic

Uses

For hand cleaning reduce bacteria that potentially can cause disease and moisture your hands.

Warnings

For external use only

Stop use and ask a doctor if irritation or rash occurs. These may be signs of a serious condition.

Keep out of reach of children

In case of accidental ingestion, seek professional assistance or contact a Poison Control Center immediately.

Directions

- Place enough product on hands to cover all surfaces. Rub hands together until dry.
- Supervise children under 6 years of age when using this product to avoid swallowing.

Other Information

- Do not store above 105 °F
- May discolor some fabrics

Inactive Ingredients

Water, Caprylic/Capric Glycerides, Ethylhexyl Palmitate, Ammonium Polyacrylate, C13-C16 Isoparaffin, Laurath-30, Phenoxyethanol, Butyrospermum Parkii (Shea Butter), Cetearyl Alcohol, Fragrance, Panthenol, Ethylhexylglycerin, Aloe Barbadensis Leaf Juice, Maltodextrin.